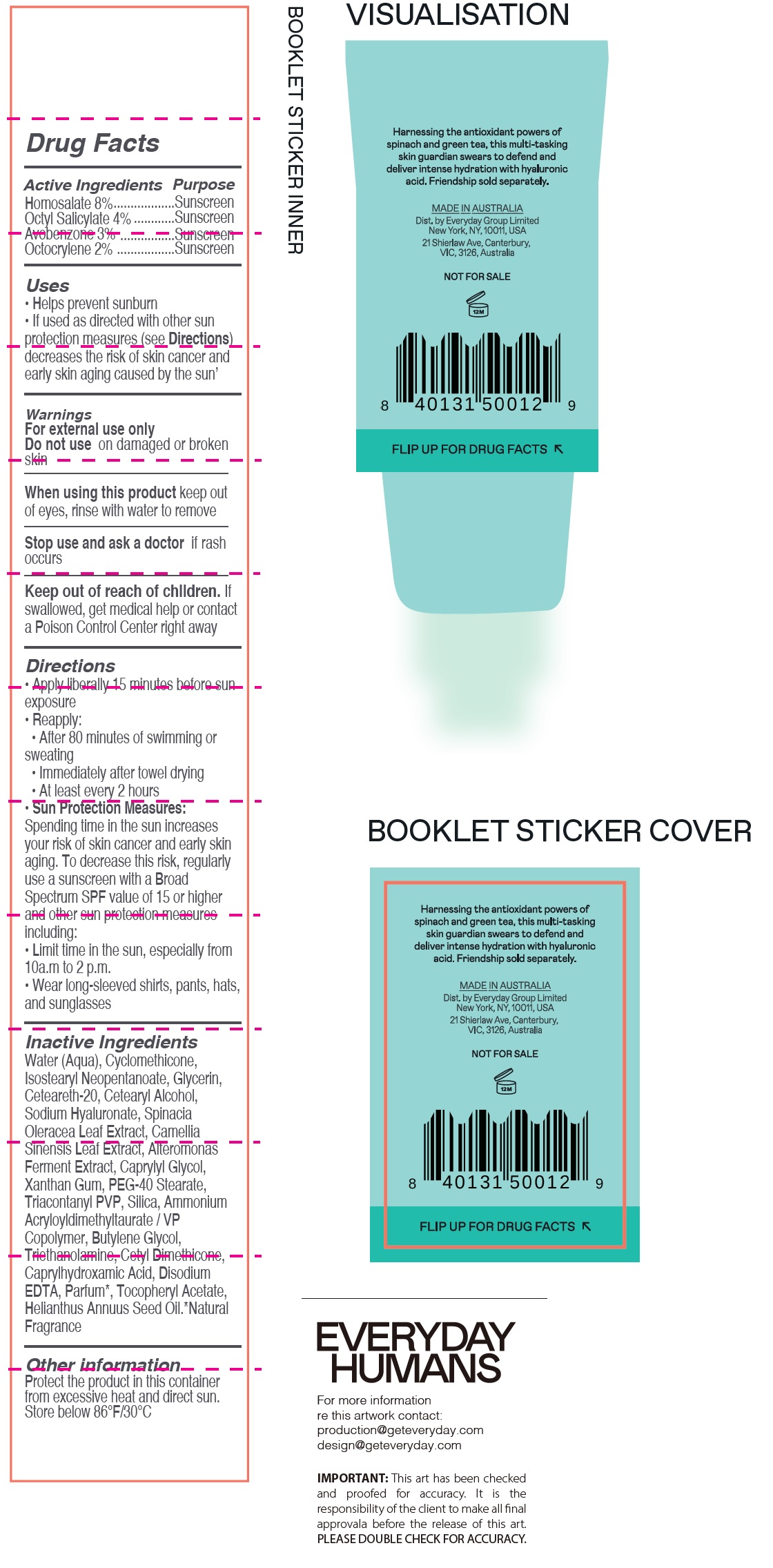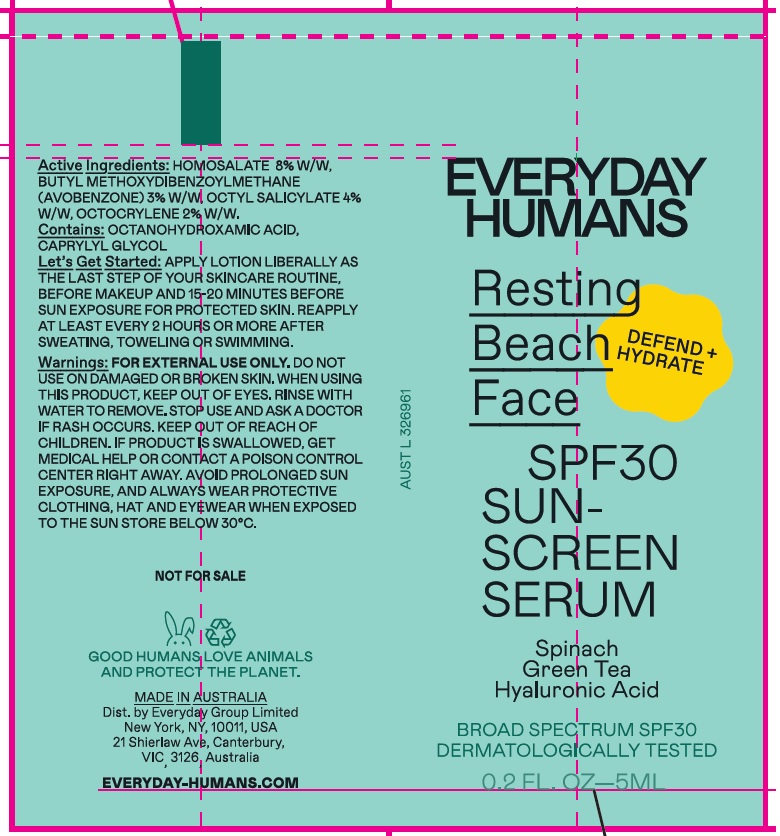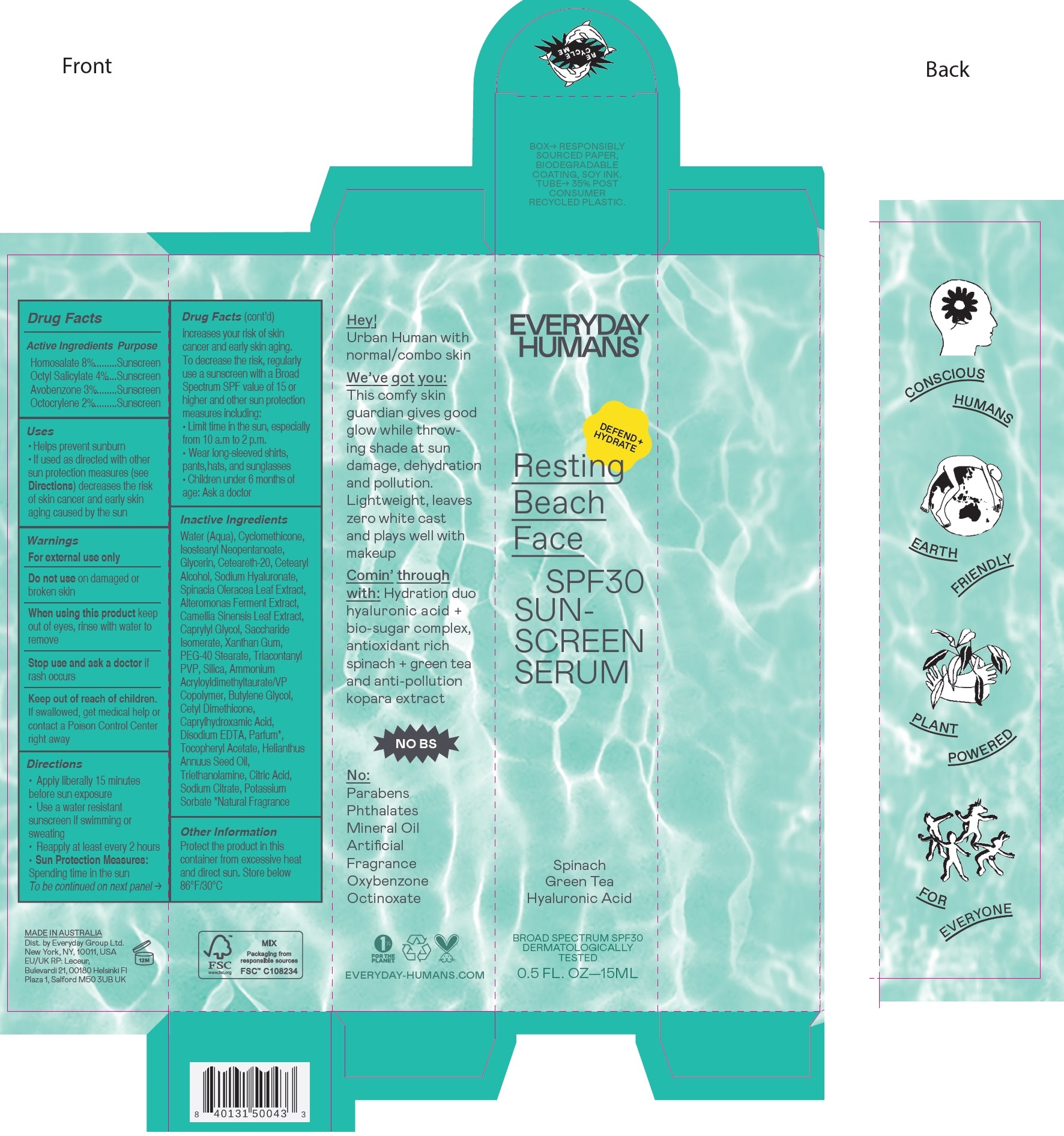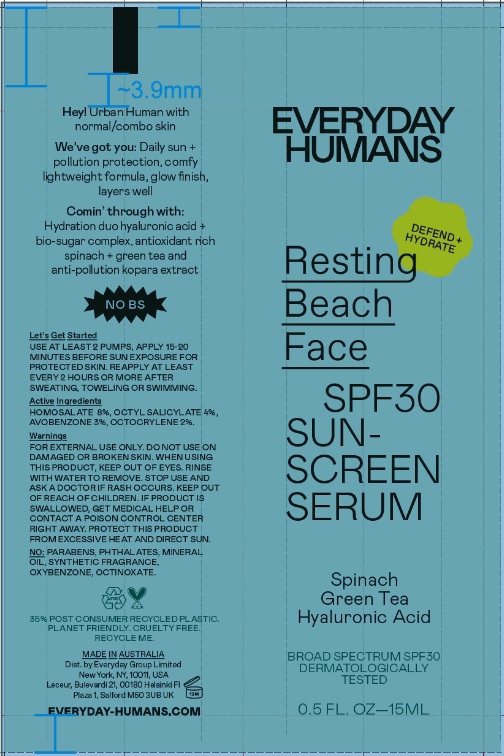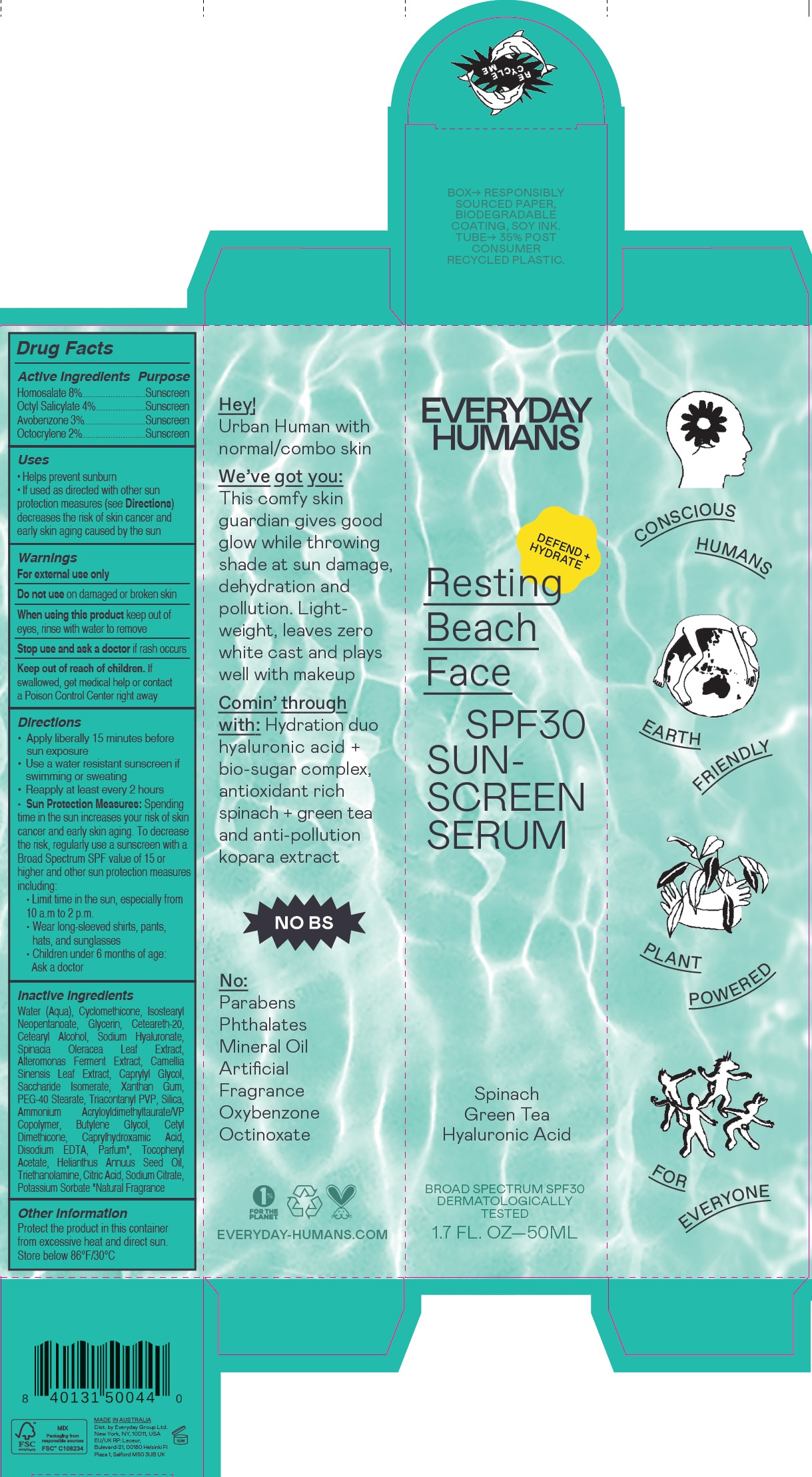 DRUG LABEL: Resting Beach Face SPF30 Anti-Pollution Sunscreen Serum
NDC: 72098-001 | Form: CREAM
Manufacturer: Everyday Group Limted
Category: otc | Type: HUMAN OTC DRUG LABEL
Date: 20251204

ACTIVE INGREDIENTS: AVOBENZONE 30 mg/1 mL; HOMOSALATE 80 mg/1 mL; OCTISALATE 40 mg/1 mL; OCTOCRYLENE 20 mg/1 mL
INACTIVE INGREDIENTS: WATER; CYCLOMETHICONE; ISOSTEARYL NEOPENTANOATE; GLYCERIN; POLYOXYL 20 CETOSTEARYL ETHER; CETOSTEARYL ALCOHOL; HYALURONATE SODIUM; ALTEROMONAS MACLEODII POLYSACCHARIDES; GREEN TEA LEAF; CAPRYLYL GLYCOL; SACCHARIDE ISOMERATE; XANTHAN GUM; PEG-40 STEARATE; TRICONTANYL POVIDONE; SILICON DIOXIDE; AMMONIUM ACRYLOYLDIMETHYLTAURATE/VP COPOLYMER; BUTYLENE GLYCOL; CAPRYLHYDROXAMIC ACID; EDETATE DISODIUM ANHYDROUS; .ALPHA.-TOCOPHEROL ACETATE; SUNFLOWER OIL; TROLAMINE; CITRIC ACID MONOHYDRATE; SODIUM CITRATE; POTASSIUM SORBATE

Resting Beach Face SPF30 Anti-Pollution Sunscreen Serum

Active ingredients

Butyl Methoxydibenzoylmethane 3%

Homosalate 8%

Octyl Salicylate 4%

Octocrylene 2%

Purpose

Sunscreen

Uses

• Helps prevent sunburn • If used as directed with other sun protection measures (see) decreases the risk of skin cancer and early skin aging caused by the sun
Directions

Warnings

For external use only

Do not use

on damaged or broken skin

When using this product

keep out of eyes, rinse with water to remove

Stop use and ask a doctor

if rash occurs

Keep out of reach of children.

If swallowed, get medical help or contact a Poison Control Center right away

Directions

• Apply liberally 15 minutes before sun exposure • Use a water resistant sunscreen if swimming or sweating • Reapply at least every 2 hours • Spending time in the sun increases your risk of skin cancer and early skin aging. To decrease the risk, regularly use a sunscreen with a Broad Spectrum SPF value of 15 or higher and other sun protection measures including: • Limit time in the sun, especially from 10 a.m to 2 p.m. • Wear long-sleeved shirts, pants, hats, and sunglasses • Children under 6 months of age: Ask a doctor
Sun Protection Measures:

Inactive ingredients

Water (Aqua), Cyclomethicone, Isostearyl Neopentanoate, Glycerin, Ceteareth-20, Cetearyl Alcohol, Sodium Hyaluronate, Spinacia Oleracea Leaf Extract, Alteromonas Ferment Extract, Camellia Sinensis Leaf Extract, Caprylyl Glycol, Saccharide Isomerate, Xanthan Gum, PEG-40 Stearate, Triacontanyl PVP, Silica, Ammonium Acryloyldimethyltaurate/VP Copolymer, Butylene Glycol, Cetyl Dimethicone, Caprylhydroxamic Acid, Disodium EDTA, Parfum*, Tocopheryl Acetate, Helianthus Annuus Seed Oil, Triethanolamine, Citric Acid, Sodium Citrate, Potassium Sorbate *Natural Fragrance

Other Information

Protect the product in this container from excessive heat and direct sun. Store below 86°F/30°C